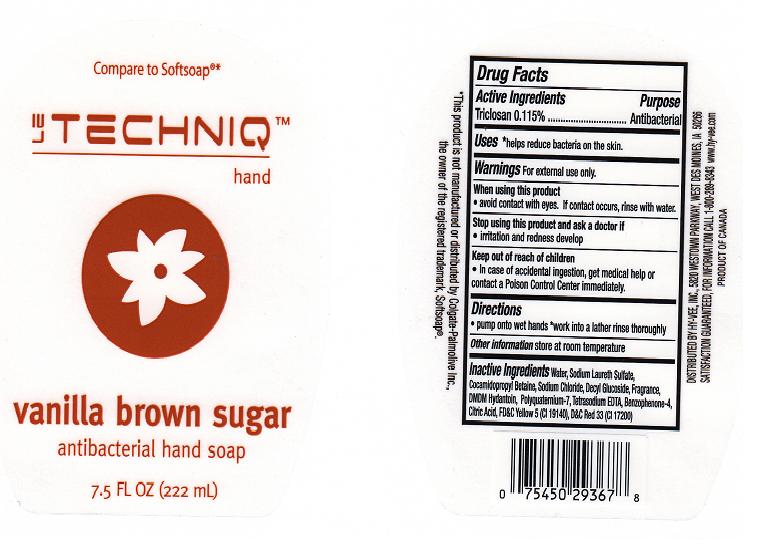 DRUG LABEL: LE TECHNIQ ANTIBACTERIAL
NDC: 42507-214 | Form: LIQUID
Manufacturer: HYVEE INC
Category: otc | Type: HUMAN OTC DRUG LABEL
Date: 20110609

ACTIVE INGREDIENTS: TRICLOSAN 0.115 mL/100 mL
INACTIVE INGREDIENTS: WATER; SODIUM LAURETH SULFATE; COCAMIDOPROPYL BETAINE; DECYL GLUCOSIDE; DMDM HYDANTOIN; POLYQUATERNIUM-7 (70/30 ACRYLAMIDE/DADMAC; 1600 KD); EDETATE SODIUM; SULISOBENZONE; CITRIC ACID MONOHYDRATE; FD&C YELLOW NO. 5; D&C RED NO. 33

DRUG FACTS

ACTIVE INGREDIENT

TRICLOSAN 0.115%

PURPOSE

ANTIBACTERIAL

USES

HELPS REDUCE BACTERIA ON THE SKIN

WARNINGS

FOR EXTERNAL USE ONLY

WHEN USING THIS PRODUCT

AVOID CONTACT WITH EYES. IF CONTACT OCCURS, RINSE THOROUGHLY WITH WATER.

STOP USING THIS PRODUCT AND ASK A DOCTOR IF

IRRITATION AND REDNESS DEVELOP

KEEP OUT OF REACH OF CHILDREN

IN CASE OF ACCIDENTAL INGESTION, GET MEDICAL HELP OR CONTACT POISON CONTROL IMMEDIATELY.

DIRECTIONS

PUMP ONTO WET HANDS. WORK INTO LATHER RINSE THOROUGHLY

OTHER INFORMATION

STORE AT ROOM TEMPERATURE

INACTIVE INGREDIENTS

WATER, SODIUM LAURETH SULFATE, COCAMIDOPROPYL BETAINE, SODIUM CHLORIDE, DECYL GLUCOSIDE, FRAGRANCE, DMDM HYDANTOIN, POLYQUATERNIUM-7, TETRASODIUM EDTA, BENZOPHENONE-4, CITRIC ACID, YELLOW 5, RED 33